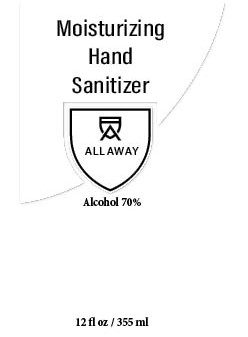 DRUG LABEL: Hand Sanitizer
NDC: 76544-710 | Form: GEL
Manufacturer: Great White Bottling Inc
Category: otc | Type: HUMAN OTC DRUG LABEL
Date: 20200422

ACTIVE INGREDIENTS: ALCOHOL 80 mL/100 mL
INACTIVE INGREDIENTS: GLYCERIN; HYDROGEN PEROXIDE; SODIUM ACRYLATE/SODIUM ACRYLOYLDIMETHYLTAURATE COPOLYMER (4000000 MW); MINERAL OIL; TRIDECETH-6; WATER

Great White Bottling Inc

Active Ingredient(s)

Alcohol 70% v/v. Purpose: Antiseptic

Purpose

Antiseptic, Hand Sanitizer

Use

Hand Sanitizer to help reduce bacteria that potentially can cause disease. For use when soap and water are not available.

Warnings

For external use only. Flammable. Keep away from heat or flame

Do not use

- in children less than 2 months of age
- on open skin wounds

When using this product keep out of eyes, ears, and mouth. In case of contact with eyes, rinse eyes thoroughly with water.

Stop use and ask a doctor if irritation or rash occurs. These may be signs of a serious condition.

Keep out of reach of children. If swallowed, get medical help or contact a Poison Control Center right away.

Directions

- Place enough product on hands to cover all surfaces. Rub hands together until dry.
- Supervise children under 6 years of age when using this product to avoid swallowing.

Other information

- Store between 15-30C (59-86F)
- Avoid freezing and excessive heat above 40C (104F)

Inactive ingredients

sodium acrylate/sodium acryloyldimethyl taurate copolymer, mineral oil, trideceth-6, glycerin, hydrogen peroxide, purified water

Package Label - Principal Display Panel

355 mL